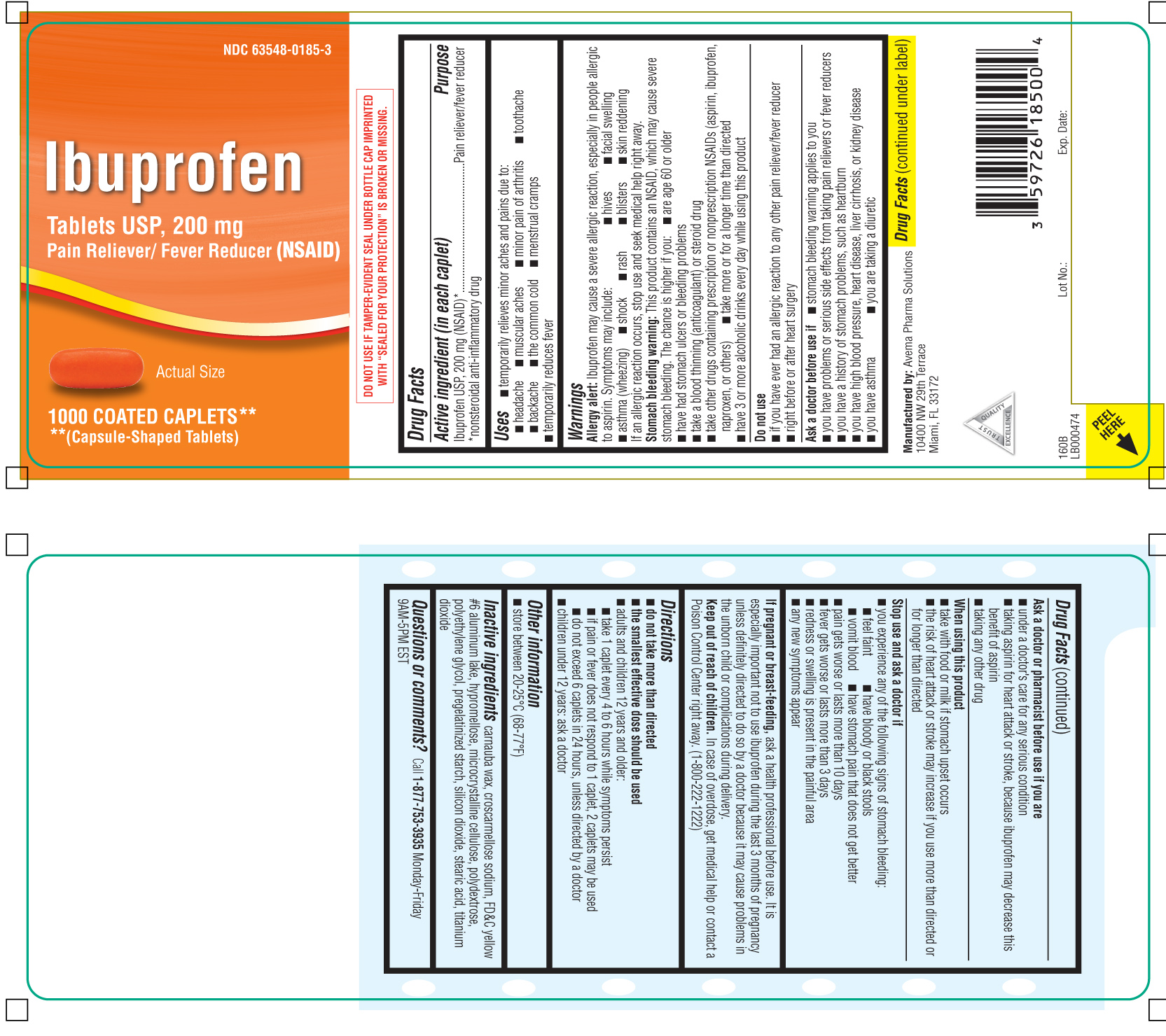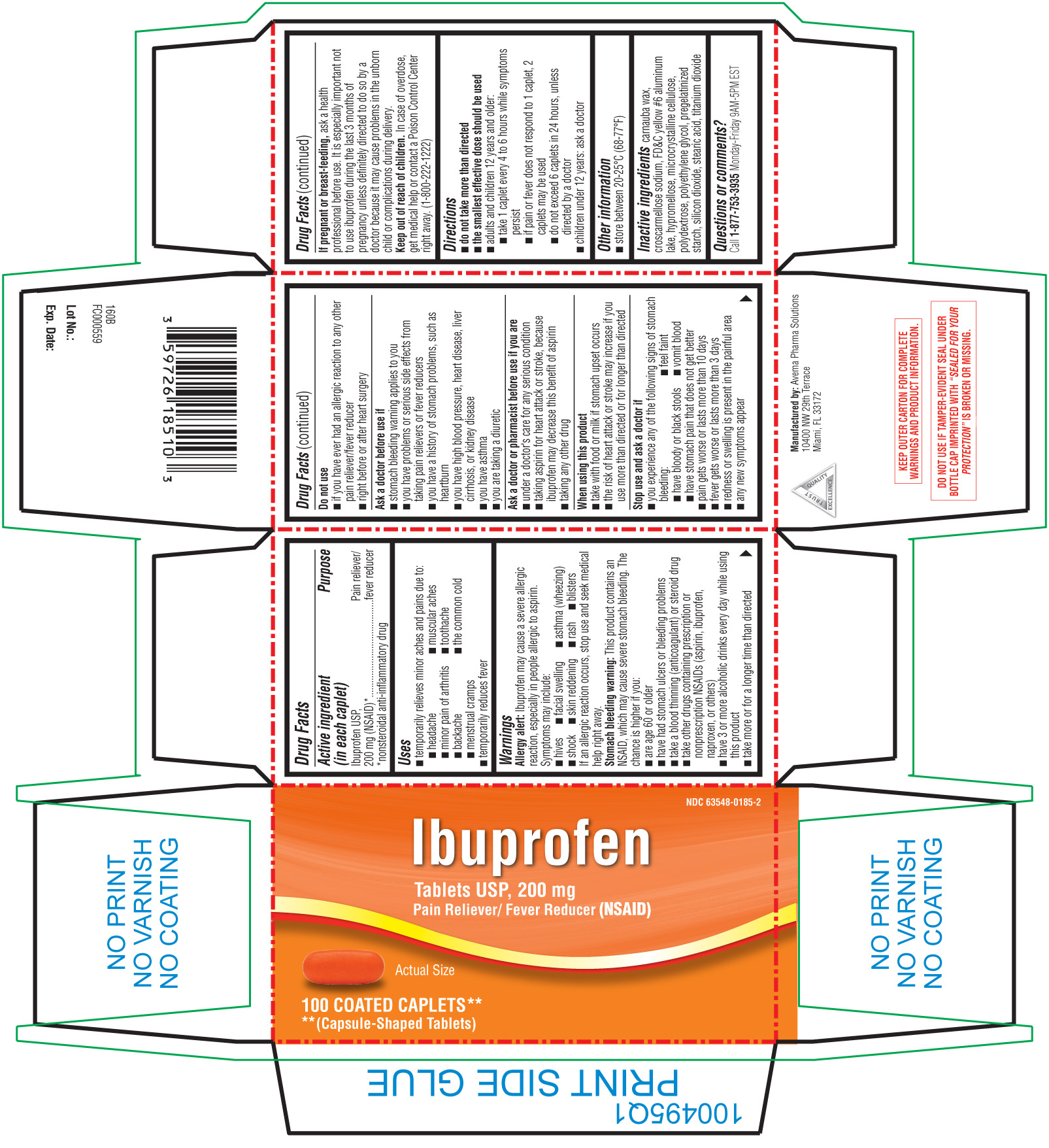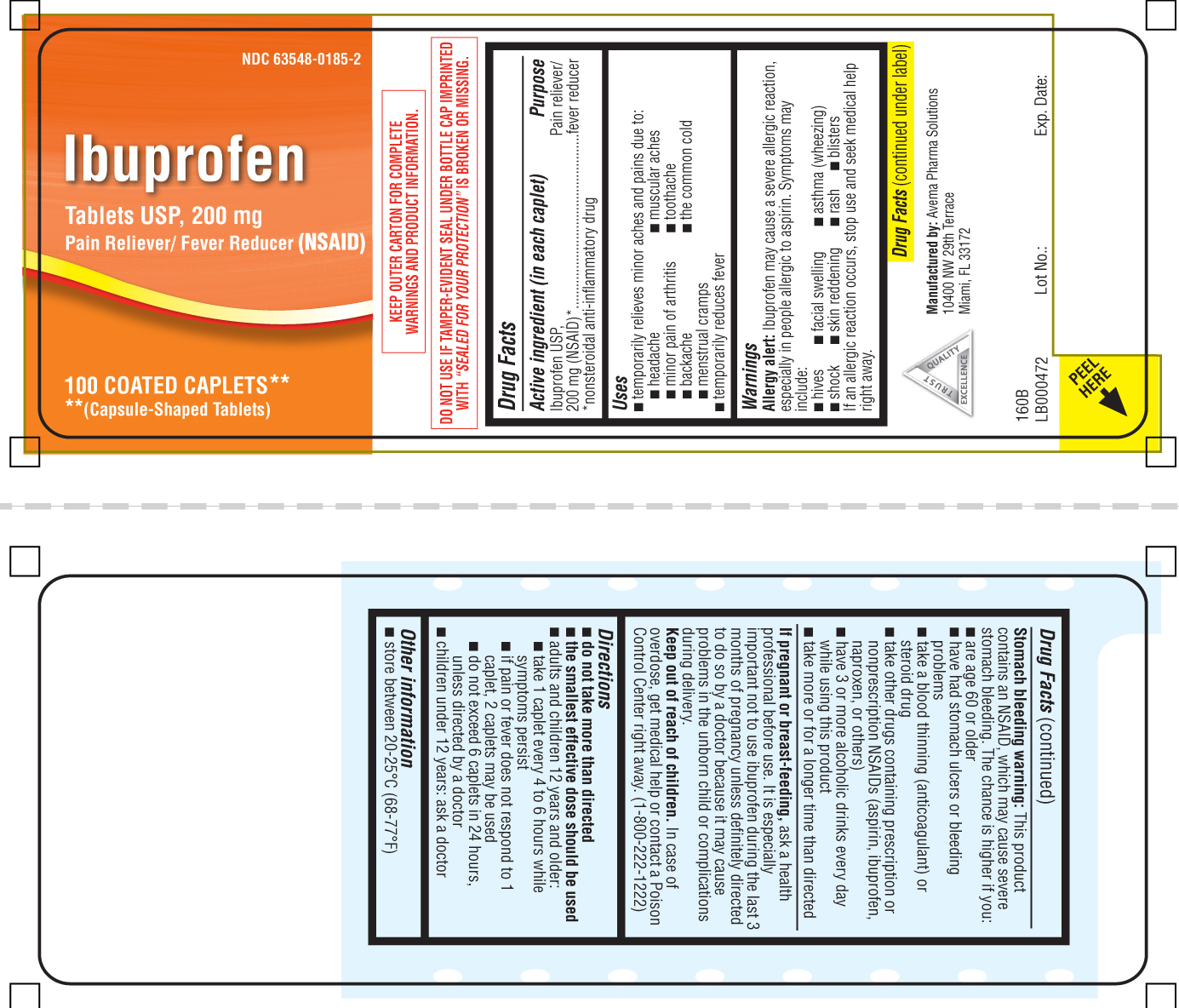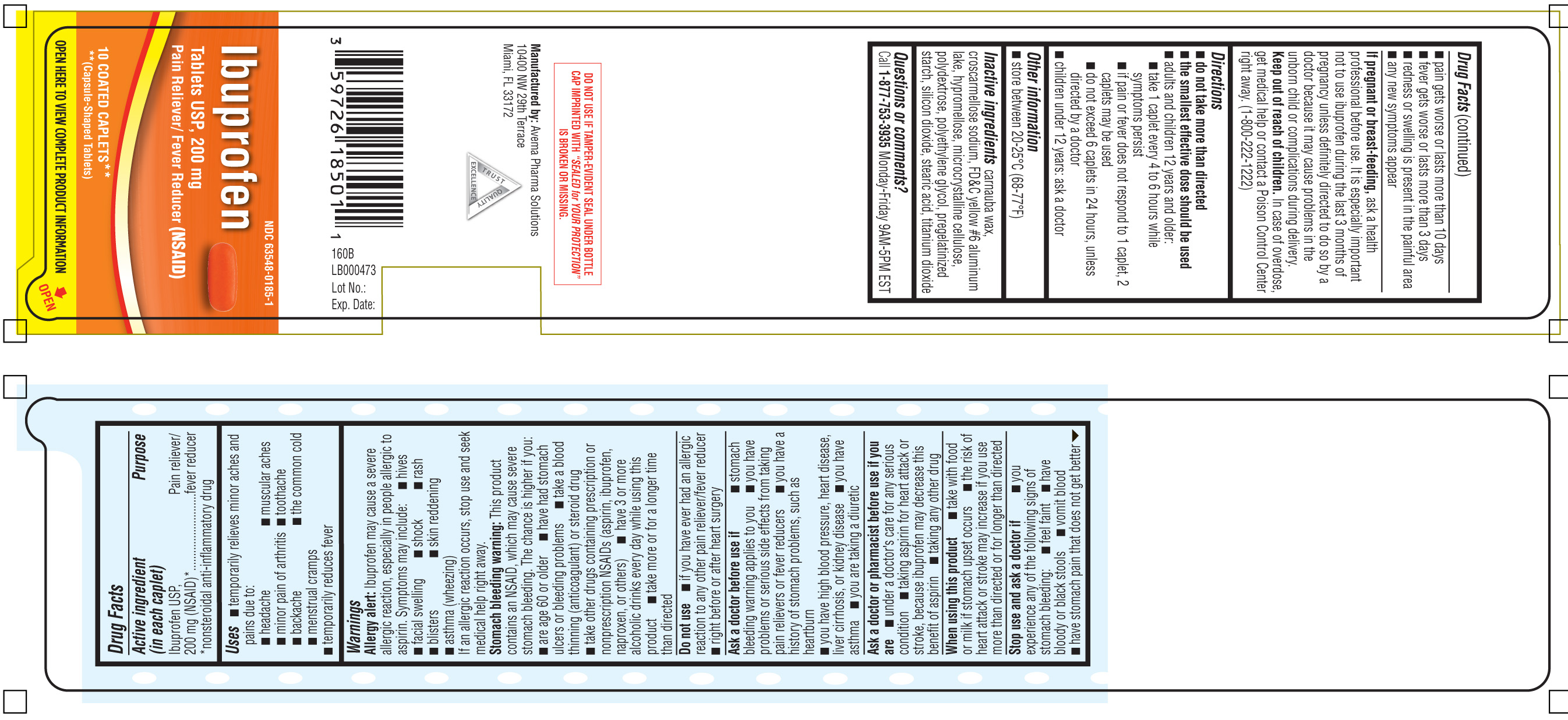 DRUG LABEL: Ibuprofen
NDC: 63548-0185 | Form: TABLET, COATED
Manufacturer: PLD Acquisitions LLC DBA Avéma Pharma Solutions
Category: otc | Type: HUMAN OTC DRUG LABEL
Date: 20250128

ACTIVE INGREDIENTS: IBUPROFEN 200 mg/1 1
INACTIVE INGREDIENTS: CARNAUBA WAX; CROSCARMELLOSE SODIUM; FD&C YELLOW NO. 6; ALUMINUM OXIDE; HYPROMELLOSES; CELLULOSE, MICROCRYSTALLINE; POLYDEXTROSE; POLYETHYLENE GLYCOL, UNSPECIFIED; STARCH, CORN; SILICON DIOXIDE; STEARIC ACID; TITANIUM DIOXIDE

DRUG FACTS

Active Ingredient (in each caplet)

Ibuprofen USP, 200 mg (NSAID)*

*nonsteroidal anti-inflammatory drug

Purpose

Pain reliever/ fever reducer

Uses

- temporarily relieves minor aches and pains due to:
  - headache
  - muscular aches
  - minor pain of arthritis
  - toothache
  - backache
  - the common cold
  - menstrual cramps
  - temporarily reduces fever

Warnings

Allergy alert: Ibuprofen may cause a severe allergic reaction, especially in people allergic to aspirin. Symptoms may include:

- hives
- facial swelling
- asthma (wheezing)
- shock
- rash
- blisters
- skin reddening

If an allergic reaction occurs, stop use an seek medical help right away.

Stomach bleeding warning: This product contains an NSAID, which may cause severe stomach bleeding. The chance is higher if you:

- are age 60 or oder
- have had stomach ulcers or bleeding problems
- take blood thinning (anticoagulant) or steroid drug
- take other drugs containing prescritpion or non-prescription NSAIDs (aspirin, ibuprofen, naproxen, or others)
- take more or for a longer time than directed.
- have 3 or more alcoholic drinks every day while using this prdouct

Do not use

- if you ever had an allergic reaction to any other pain reliever/fever reducer
- right before or after heart surgery

Ask a doctor before use if

- stomach bleeding warning applies to you
- you have problems or serious side effects from taking pain relievers or fever reducers
- you have a history of stomach problems such as heartburn
- you have high blood pressure, heart disease, liver cirrhosis, or kidney disease
- you have asthma
- you are taking a diuretic.

Ask a doctor or pharmacist before use if you are

- under a doctor's care for any serious condition
- taking aspirin for heart attack or stroke, because ibuprofen may decrease this benefit of aspirin
- taking any other drug.

When using this product

- take with food or milk if stomach upset occurs
- the risk of heart attack or stroke may increase if you use more than directed or for longer than directed.

Stop use and ask a doctor if

- You experience any of the following signs of stomach bleeding:
  - feel faint
  - have bloody or black stools
  - vomit blood
  - have stomach pain that does not get better
  - pain gets worse or last more than 10 days
  - fever gets worse or last more than 3 days
  - redness or swelling is present in the painful area
  - any new symptoms appear

If pregnant or breast-feeding

ask a health professional before use. It is especially important not to use ibuprofen druing the last 3 months of pegnancy unless defintely directed to do so by a doctor because it may cause problems in the unborn child or complications during delivery.

Keep out of reach of children.

In case of overdose, get medical help or contact a Poison Control Center right away (1-800-222-1222)

Directions

- do not take more than directed
- the smallest effective dose should be used
- adults and children 12 years and older:
  - take 1 caplet every 4 to 6 hours while symptoms persist
  - if pain or fever does not respond to 1 caplet, 2 caplets may be used
  - do not exceed 6 caplets in 24 hours, unless directed by a doctor
- children under 12 years : ask a doctor

Other information

- store between 20o- 25o C (68o- 77o F)

Inactive Ingredients

carnauba wax, croscarmellose sodium, FD&C yellow #6 aluminium lake, hypromellose, microcrystalline cellulose, polydextrose, polyethylene glycol, pregelatinized starch, silicon dioxide, stearic acid, titanium dioxide.

Questions or comments?

Call 1-877-753-3935 Monday-Friday 9AM-5PM EST

Principal Display Panel

Ibuprofen Tablets USP, 200 mg

Pain Reliever/ Fever Reducer (NSAID)

Coated Caplets**

**(Capsule-Shaped Tablets)

DO NOT USE IF TAMPER-EVIDENT SEAL UNDER BOTTLE CAP IMPRINTED WITH "SEALED FOR YOUR PROTECTION" IS BROKEN OR MISSING

Manufactured by: Avema Pharma Solutions

10400 NW 29th Terrace

Miami, FL 33172

Product Label

Ibuprofen 200 mg orange Caplets
Ibuprofen 200 mg orange Caplets
Ibuprofen 200 mg orange Caplets
Ibuprofen 200 mg orange Caplets